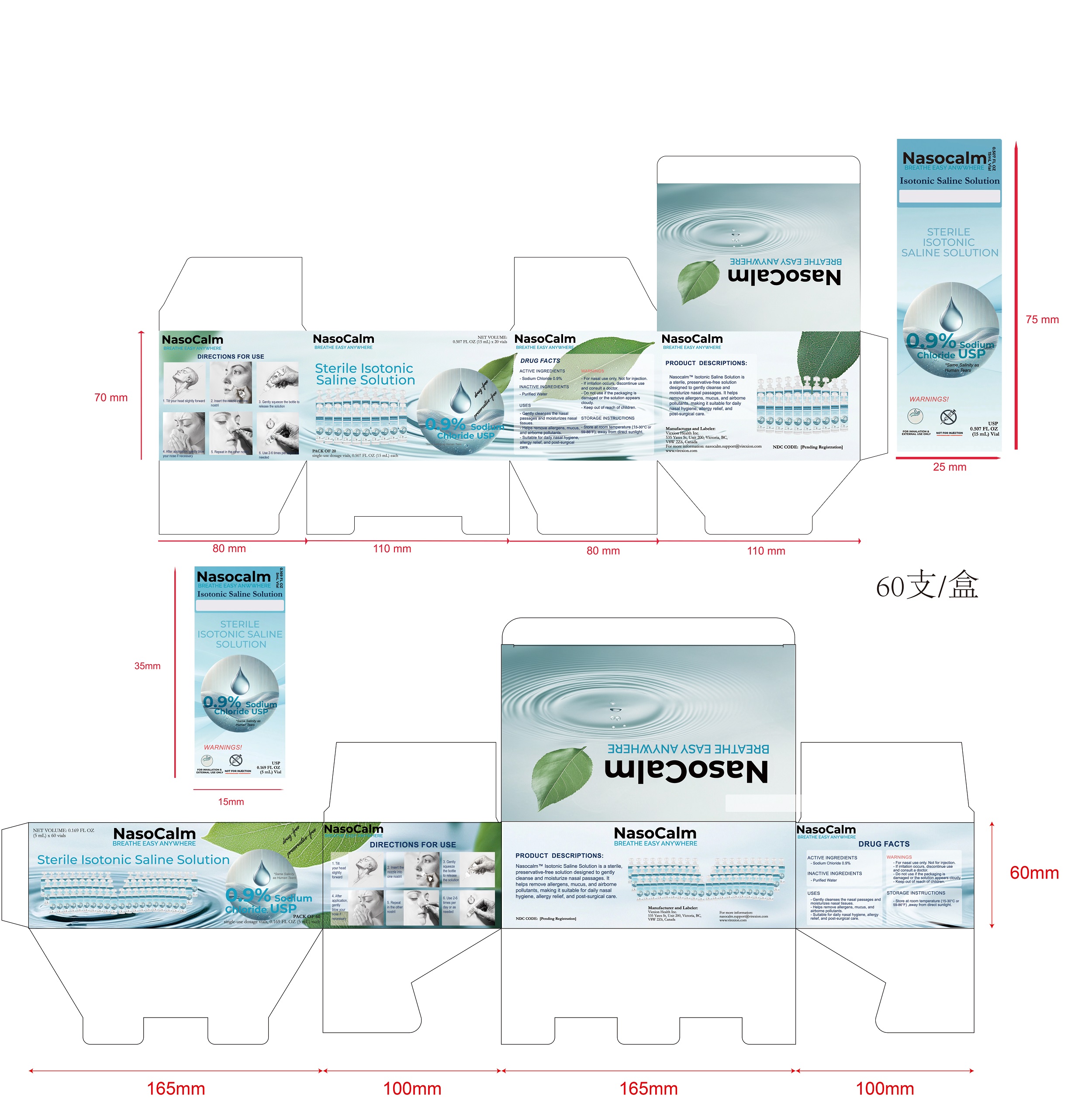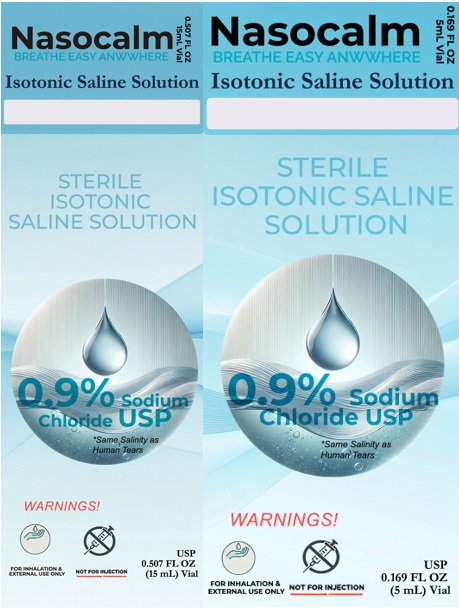 DRUG LABEL: Nasocalm
NDC: 85436-002 | Form: SOLUTION
Manufacturer: Virexion Health Inc.
Category: otc | Type: HUMAN OTC DRUG LABEL
Date: 20250328

ACTIVE INGREDIENTS: SODIUM CHLORIDE 0.9 mg/100 mg
INACTIVE INGREDIENTS: WATER

ACTIVE INGREDIENT

Sodium Chloride (NaCl) 0.9%

PURPOSE

Hydrates, soothes, and clears nasal passages, relieves mild congestion, and flushes out allergens, dust, and pollutants, suitable for daily nasal hygiene for all ages.

INDICATIONS AND USAGE

1. Gently cleanses the nasal passages and moisturizes nasal tissues.
2. Helps remove allergens, mucus, and airborne pollutants.
3. Suitable for daily nasal hygiene, allergy relief, and post-surgical care.

WARNINGS

For nasal use only. Not for injections.

Do not use if the packaging is damaged or the solution appears cloudy.

Stop use and consult a doctor if irritation or infection occurs.

Keep out of reach of children.

Directions

1. Tilt your head slightly forward

2. Insert the nozzle into one nostril

3. Gently squeeze the bottle to release the solution

4. After application, gently blow your nose if necessary

5. Repeat in the other nostril

6. Use 2-6 times per day or as needed

7. Children and infants must be used under adult supervision. For children under 5 years old, please follow the advice of a healthcare professional

INACTIVE INGREDIENT

Purified water USP

STORAGE AND HANDLING

1. Store at room temperature (15-30°C or 59-86°F).

2. Protect from extreme heat and direct sunlight.